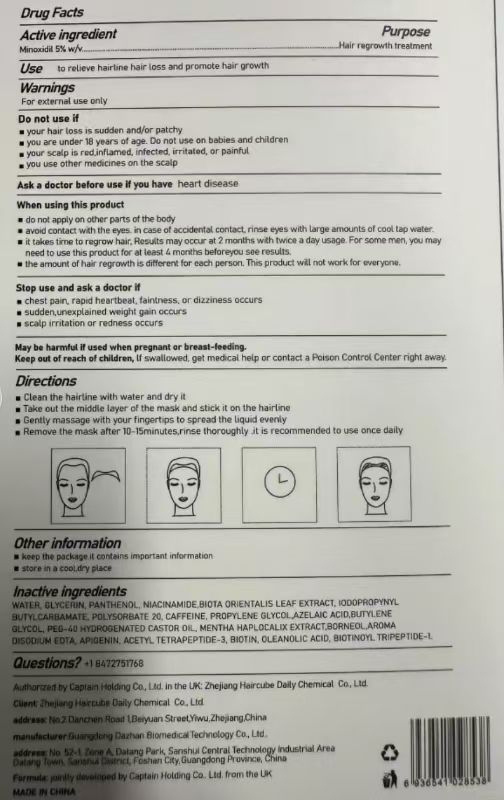 DRUG LABEL: HAIRLINE MASK
NDC: 84979-016 | Form: PASTE
Manufacturer: Guangdong Dazhan Biomedical Technology Co., Ltd
Category: otc | Type: HUMAN OTC DRUG LABEL
Date: 20241121

ACTIVE INGREDIENTS: MINOXIDIL 1.25 g/1.25 g
INACTIVE INGREDIENTS: CAFFEINE; BIOTIN; GLYCERIN; PANTHENOL; BUTYLENE GLYCOL; BORNEOL; POLYSORBATE 20; WATER; PEG-40 HYDROGENATED CASTOR OIL; OLEANOLIC ACID; IODOPROPYNYL BUTYLCARBAMATE; APIGENIN; AZELAIC ACID; NIACINAMIDE

WARNINGS

For external use only

Avoid contact with eyes. In case of accidental contact, rinse eyes thoroughly with water.

Indications and Usage

For women:
This product is intended to promote hair regrowth and reduce hair thinning along the hairline.

Stop Use and Ask a Doctor if

You experience:

Severe scalp irritation, redness, or swelling.
Unusual symptoms such as dizziness, fainting, or chest pain.
Swelling in the hands or feet.
Persistent or worsening hair loss after regular use.

No improvement in hair regrowth is observed after 4 months of consistent use as directed.

You develop an allergic reaction (e.g., rash, itching, or swelling).

Hair loss occurs in patches, suddenly increases, or is accompanied by other medical symptoms.

Keep Out of Reach of Children

This product is not intended for use by children under 18 years of age.
If swallowed, get medical help or contact a Poison Control Center immediately.

DOSAGE AND ADMINISTRATION

Ensure the scalp is clean and dry before application.
Remove the adhesive backing from the patch and apply directly to the targeted area along the hairline.
Press gently to secure the patch in place.

INACTIVE INGREDIENT

WATER

GLYCERIN

PANTHENOL

NIACINAMIDE

BIOTA ORIENTALIS LEAF EXTRACT

IODOPROPYNYL BUTYLCARBAMATE

POLYSORBATE 20

CAFFEINE

PROPYLENE GLYCOL

AZELAIC ACID

BUTYLENE GLYCOL

PEG-40 HYDROGENATED CASTOR OIL

MENTHA HAPLOCALIX EXTRACT

BORNEOL

AROMA

DISODIUM EDTA

APIGENIN

ACETYL TETRAPEPTIDE-3

BIOTIN

OLEANOLIC ACID

BIOTINOYL TRIPEPTIDE-1

DOSAGE AND ADMINISTRATION

Clean and dry the area along the hairline before application.
Remove the protective backing from the patch.
Place the patch gently on the targeted area of thinning hair or receding hairline.
Press down firmly to ensure proper adhesion.

PURPOSE

Hair Regrowth Treatment
Helps to promote hair regrowth and prevent further hair loss.